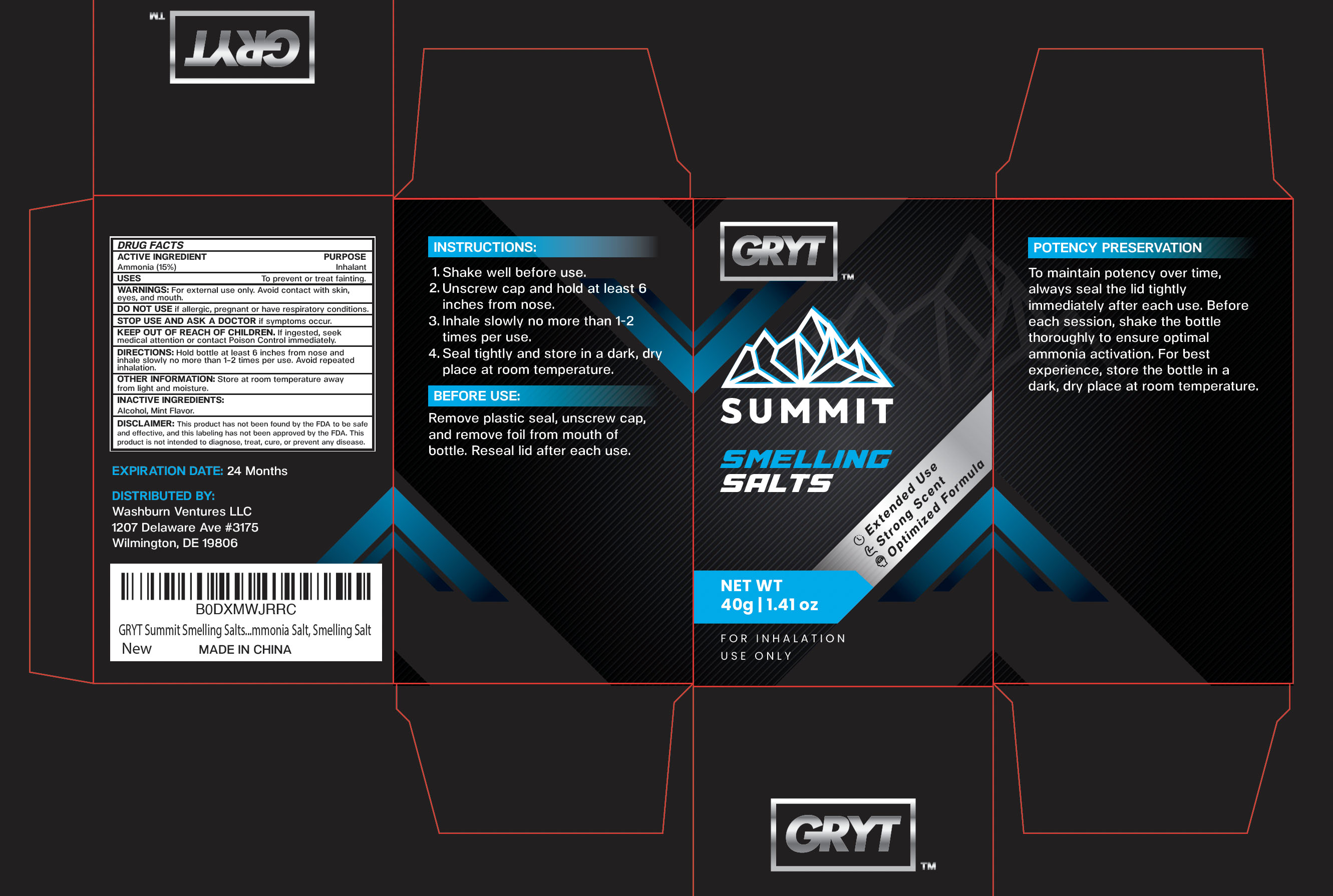 DRUG LABEL: Summit Smelling Salts
NDC: 85764-001 | Form: INHALANT
Manufacturer: Washburn Ventures LLC
Category: otc | Type: HUMAN OTC DRUG LABEL
Date: 20250616

ACTIVE INGREDIENTS: AMMONIA 15 g/100 g
INACTIVE INGREDIENTS: ALCOHOL; MINT

ACTIVE INGREDIENT

Ammonia (15%)

PURPOSE

Inhalant

INDICATIONS AND USAGE

To prevent or treat fainting.

WARNINGS

WARNINGS: For external use only. Avoid contact with skin, eyes, and mouth.

DO NOT USE

if allergic, pregnant or have respiratory conditions.

WHEN USING

INSTRUCTIONS:

1.Shake well before use.

2.Unscrew cap and hold at least 6 inches from nose.

3. Inhale slowly no more than 1-2 times per use.

4.Seal tightly and store in a dark, dry place at room temperature.

BEFORE USE:

Remove plastic seal, unscrew cap, and remove foil from mouth of bottle. Reseal lid after each use.

POTENCY PRESERVATION :

To maintain potency over time, always seal the lid tightly immediately after each use. Before each session, shake the bottle thoroughly to ensure optimal ammonia activation. For best experience, store the bottle in a dark, dry place at room temperature.

STOP USE AND ASK A DOCTOR if symptoms occur.

KEEP OUT OF REACH OF CHILDREN. If ingested, seek medical attention or contact Poison Control immediately.

DOSAGE AND ADMINISTRATION

DIRECTIONS: Hold bottle at least 6 inches from nose and inhale slowly no more than 1-2 times per use. Avoid repeated inhalationy

OTHER INFORMATION: Store at room temperature away from light and moisture.

INACTIVE INGREDIENT

Alcohol, Mint Flavor.